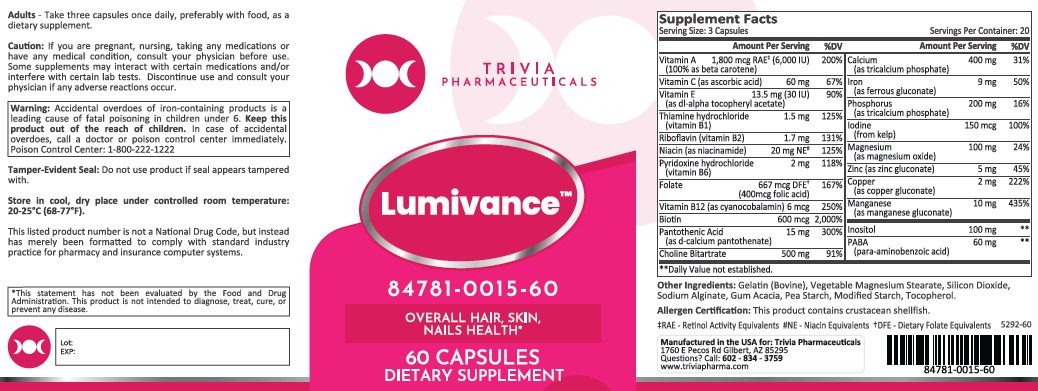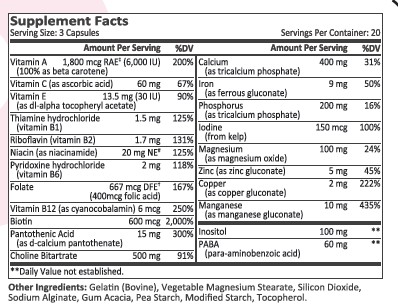 DRUG LABEL: Lumivance
NDC: 84781-015 | Form: CAPSULE
Manufacturer: Trivia Pharmaceuticals, LLC
Category: other | Type: Dietary Supplement
Date: 20251006

ACTIVE INGREDIENTS: BETA CAROTENE 600 ug/1 1; ASCORBIC ACID 20 mg/1 1; BIOTIN 200 ug/1 1; CALCIUM 133.333 mg/1 1; CALCIUM PANTOTHENATE 5 mg/1 1; CHOLINE BITARTRATE 166.667 mg/1 1; COPPER GLUCONATE 0.667 mg/1 1; CYANOCOBALAMIN 2 ug/1 1; FERROUS GLUCONATE 3 mg/1 1; FOLIC ACID 133.333 ug/1 1; INOSITOL 33.333 mg/1 1; MACROCYSTIS PYRIFERA (KELP) 50 ug/1 1; MAGNESIUM OXIDE 33.333 1/1 1; MANGANESE GLUCONATE 3.333 1/1 1; NIACIN 6.667 1/1 1; TRICALCIUM PHOSPHATE 66.667 mg/1 1; PYRIDOXINE HYDROCHLORIDE 0.667 mg/1 1; RIBOFLAVIN 0.567 1/1 1; THIAMINE HYDROCHLORIDE 0.5 1/1 1; .ALPHA.-TOCOPHEROL ACETATE, DL- 4.5 mg/1 1; ZINC GLUCONATE 1.667 mg/1 1; AMINOBENZOIC ACID 20 mg/1 1

Lumivance

HEALTH CLAIM:

Lumivance Vitamin Capsules

DESCRIPTION:

Lumivance Multivitamin Capsules are clear capsules dispensed in plastic bottles of 60 ct.

84781-0015-60

Reserved for Professional Recommendation

Lumivance Vitamin Capsules are an orally administered vitamin to provide significant amounts of vitamins to supplement the diet, and to help assure that nutritional deficiencies of these vitamins will not develop.

This listed product is not a National Drug Code, but instead has merely been formatted to comply with standard industry practice for pharmacy and insurance computer systems.

These statements have not been evaluated by the Food and Drug Administration. This product is not intended to diagnose, treat, cure or prevent any disease.

All prescriptions using this product shall be pursuant to state statutes as applicable. This is not an Orange Book product. This product may be administered only under a physician’s supervision. There are no implied or explicit claims on therapeutic equivalence.

Manufactured for:

Trivia Pharmaceuticals, LLC

Gilbert, AZ

WARNINGS:

Caution: If you are pregnant, nursing, taking any medications or have any medical condition, consult your physician before use. Some supplements may interact with certain medications and/or interfere with certain lab tests. Discontinue use and consult your physician if any adverse reactions occur.

This product is contraindicated in patients with a known hypersensitivity to any of the ingredients.

These statements have not been evaluated by the Food and Drug Administration. This product is not intended to diagnose, treat, cure, or prevent any disease.

DOSAGE AND ADMINISTRATION:

Usual adult dose is 3 capsules by mouth daily once daily, preferably with food, as a dietary supplement.

PRECAUTIONS:

CONTRAINDICATIONS
This product is contraindicated in patients with known hypersensitivity to any of the ingredients.

PRECAUTIONS
This product is contraindicated in patients with a known hypersensitivity to any of the ingredients.

ADVERSE REACTIONS
Allergic sensitizations have been reported following oral administration of folic acid. Consult your physician immediately if adverse side effects occur.

Warning: Accidental overdoses of iron-containing products is a leading cause of fatal poisoning in children under 6. Keep this product out of the reach of children. In case of accidental overdoses, call a doctor or poison control immediately. Poison Control Center: 1-800-222-1222

STORAGE:

Store at 20° to 25°C (68° to 77°F); excursions permitted to 15° to 30°C (59° to 86°F). [See USP Controlled Room Temperature.] Protect from light and moisture. Do not use product if seal appears tampered with.